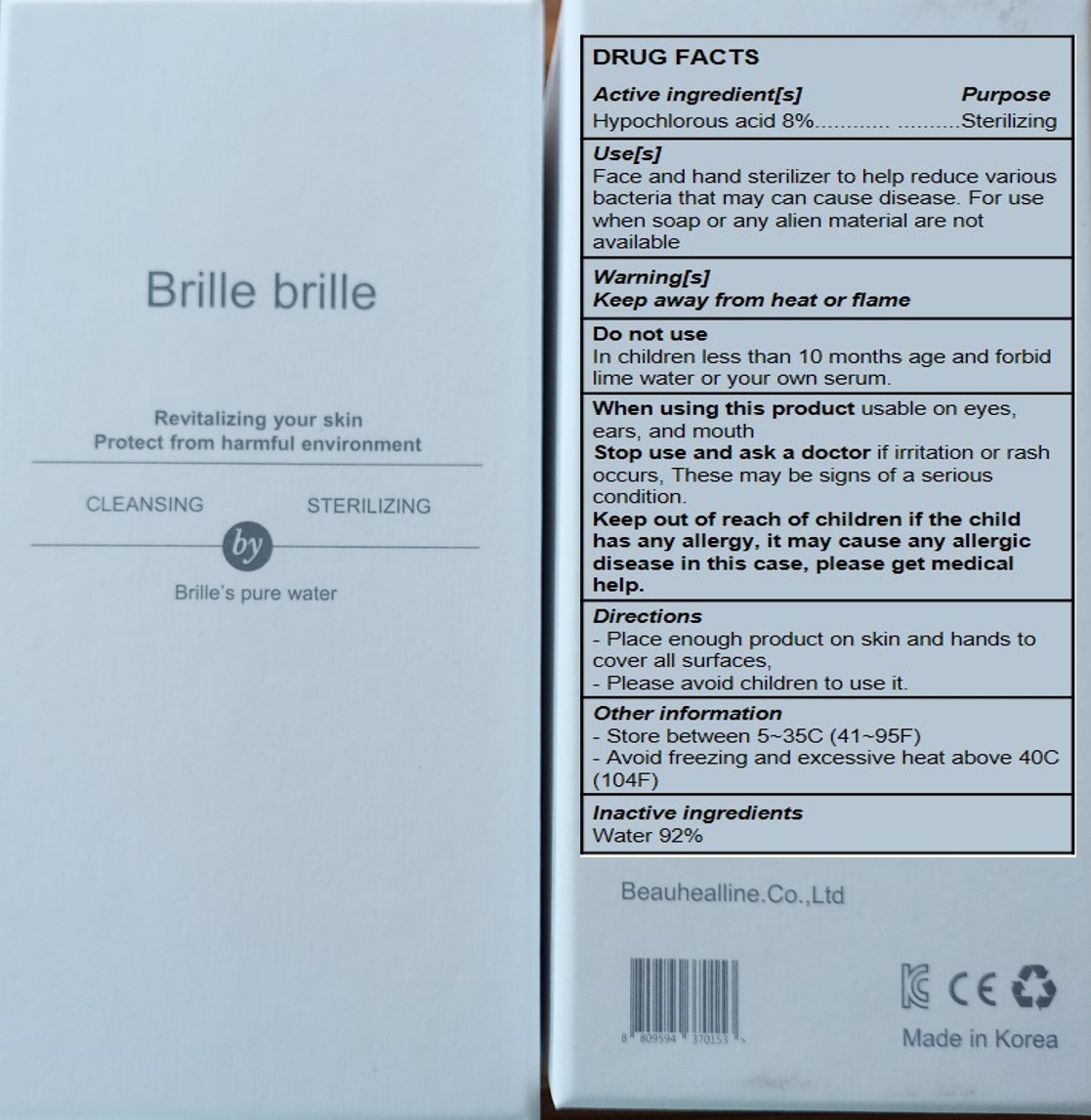 DRUG LABEL: Brille brille sterilizing water mist
NDC: 81546-301 | Form: LIQUID
Manufacturer: Beauhealline Co., Ltd
Category: otc | Type: HUMAN OTC DRUG LABEL
Date: 20210708

ACTIVE INGREDIENTS: HYPOCHLOROUS ACID 8 mg/100 mL
INACTIVE INGREDIENTS: WATER

Brille brille sterilizing water mist 81546-301

Active ingredient[s]

Hypochlorous acid

Purpose

Sterilizing

Use[s]

Face and hand sterilizer to help reduce various bacteria that may can cause disease. For use when soap or any alien material are not available

Warning[s]

Keep away from heat or flame

Do not use

In children less than 10 months age and forbid lime water or your own serum.

When using this product

usable on eyes, ears, and mouth

Stop use and ask a doctor

if irritation or rash occurs, These may be signs of a serious condition.

Keep out of reach of children

if the child has any allergy, it may cause any allergic disease in this case, please get medical help.

Directions

-Place enough product on skin and hands to cover all surfaces,
-Please avoid children to use it.

Other information

-Store between 5~35C (41~95F)
-Avoid freezing and excessive heat above 40C (104F)

Inactive ingredients

Water